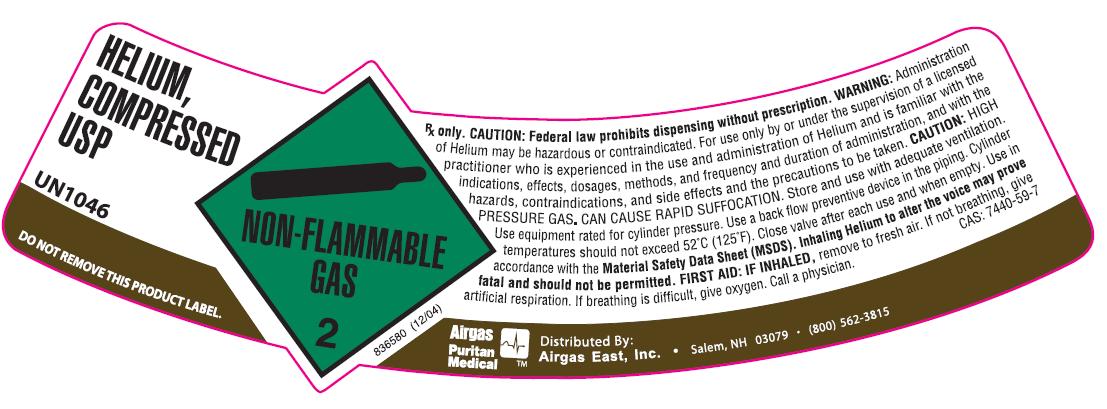 DRUG LABEL: Helium
NDC: 25543-011 | Form: GAS
Manufacturer: Airgas East, Inc.
Category: prescription | Type: HUMAN PRESCRIPTION DRUG LABEL
Date: 20100623

ACTIVE INGREDIENTS: Helium 999 mL/1 L

helium

PACKAGE LABEL

HELIUM, COMPRESSED USP UN1046
DO NOT REMOVE THIS PRODUCT LABEL. NON-FLAMMABLE GAS 2 836580 (12/04)
Rx only. CAUTION: Federal law prohibits dispensing without prescription. WARNING: Administration of Helium may be hazardous or contraindicated. For use only by or under supervision of a licensed practitioner who is experienced in the use and administration of Helium and is familiar with the indications, effects, dosages, methods, and frequency and duration of administration, and with the hazards, contraindications, and side effects and the precautions to be taken. CAUTION: HIGH PRESSURE GAS, CAN CAUSE RAPID SUFFOCATION. Store and use with adequate ventilation. Use equipment rated for cylinder pressure. Use a back flow preventive device in the piping. Cylinder temperatures should not exceed 52C (125F). Close valve after each use and when empty. Use in accordance with the Material Safety Data Sheet (MSDS). Inhaling Helium to alter the voice may prove fatal and should not be permitted. FIRST AID: IF INHALED, remove to fresh air. If not breathing, give artificial respiration. If breathing is difficult, give oxygen. Call a physician. CAS: 7440-59-7
AIRGAS PURITAN MEDICAL AIRGAS EAST, Inc. Salem, NH 03079 (800) 562-3815